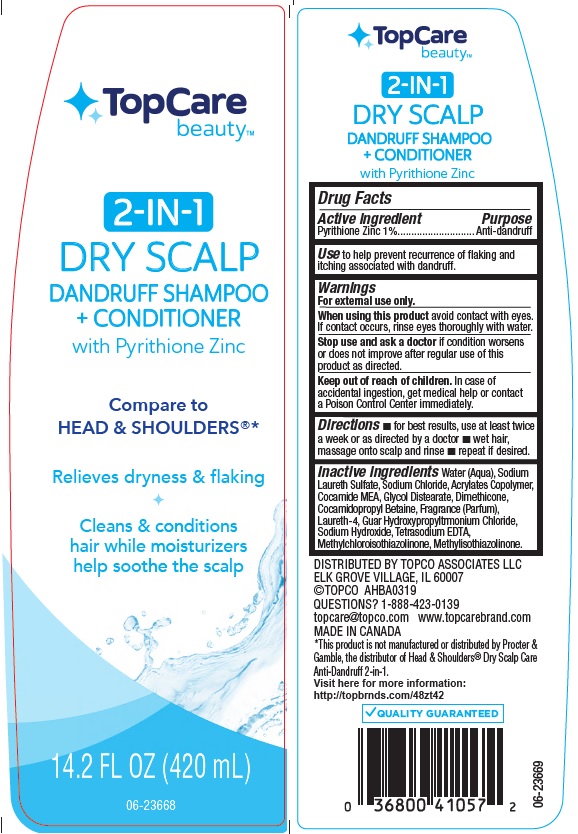 DRUG LABEL: TopCare 2 in 1 Dry Scalp Dandruff
NDC: 36800-798 | Form: SHAMPOO
Manufacturer: Topco Associates LLC
Category: otc | Type: HUMAN OTC DRUG LABEL
Date: 20190927

ACTIVE INGREDIENTS: PYRITHIONE ZINC 10 mg/1 mL
INACTIVE INGREDIENTS: WATER; SODIUM LAURETH SULFATE; SODIUM CHLORIDE; METHACRYLIC ACID - METHYL METHACRYLATE COPOLYMER (1:1); COCO MONOETHANOLAMIDE; GLYCOL DISTEARATE; DIMETHICONE; COCAMIDOPROPYL BETAINE; LAURETH-4; GUAR HYDROXYPROPYLTRIMONIUM CHLORIDE (1.7 SUBSTITUENTS PER SACCHARIDE); SODIUM HYDROXIDE; EDETATE SODIUM; METHYLCHLOROISOTHIAZOLINONE; METHYLISOTHIAZOLINONE

Active ingredient

Pyrithione Zinc 1%

Purpose

Antidandruff

Use

to help prevent recurrence of flaking and itching associated with dandruff.

Warnings

For external use only.

When using this product

avoid contact with eyes. If contact occurs, rinse eyes thoroughly with water.

Stop use and ask a doctor if

conditioner worsens or does not improve after regular use of this product as directed.

Keep out of reach of children.

In case of accidental ingestion, get medical help or contact a Poison Control Center immediately.

Directions

- for best results, use at least twice a week, or as directed by a doctor
- wet hair, massage onto scalp and rinse
- repeat if desired

Inactive ingredients

Water (Aqua), Sodium Laureth Sulfate, Sodium Chloride, Acrylates Copolymer, Cocamide MEA, Glycol Distearate, Dimethicone, Cocamidopropyl Betaine, Fragrance (Parfum), Laureth-4, Guar Hydroxypropyltrimonium Chloride, Sodium Hydroxide, Tetrasodium EDTA, Methylchloroisothiazolinone, Methylisothiazolinone.